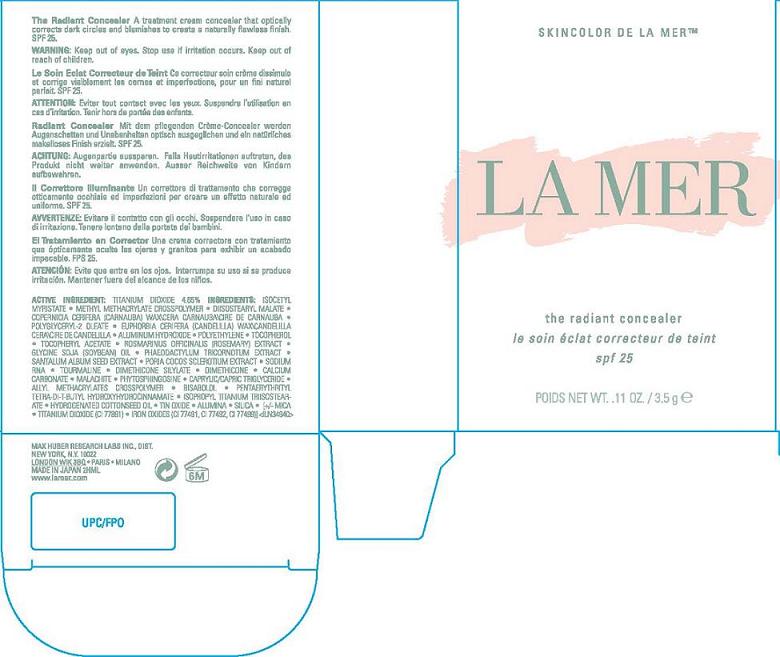 DRUG LABEL: THE RADIANT CONCEALER
NDC: 65966-010 | Form: CREAM
Manufacturer: MAX HUBER RESEARCH LAB INC
Category: otc | Type: HUMAN OTC DRUG LABEL
Date: 20110706

ACTIVE INGREDIENTS: TITANIUM DIOXIDE 4.65 g/100 g
INACTIVE INGREDIENTS: METHYL METHACRYLATE; CARNAUBA WAX; CANDELILLA WAX; ALUMINUM HYDROXIDE; ALPHA-TOCOPHEROL; ALPHA-TOCOPHEROL ACETATE; ROSEMARY; SOYBEAN OIL; SEAWEED; FU LING; MAGNESIUM SILICATE; DIMETHICONE; SILICON DIOXIDE; CALCIUM CARBONATE; CUPRIC CARBONATE; MEDIUM-CHAIN TRIGLYCERIDES; LEVOMENOL;  PENTAERYTHRITOL TETRAKIS(3-(3,5-DI-TERT-BUTYL-4-HYDROXYPHENYL)PROPIONATE); HYDROGENATED COTTONSEED OIL; STANNIC OXIDE; ALUMINUM OXIDE; MICA; FERRIC OXIDE RED

ACTIVE INGREDIENT: TITANIUM DIOXIDE 4.65%

INACTIVE INGREDIENT

INGREDIENTS: ISOCETYL MYRISTATE [] METHYL METHACRYLATE CROSSPOLYMER [] DIISOSTEARYL MALATE [] COPERNICIA CERIFERA (CARNAUBA) WAX\CERA CARNAUBA\CIRE DE CARNAUBA [] POLYGLYCERYL-2 OLEATE [] EUPHORBIA CERIFERA (CANDELILLA) WAX\CANDELILLA CERA\CIRE DE CANDELILLA [] ALUMINUM HYDROXIDE [] POLYETHYLENE [] TOCOPHEROL [] TOCOPHERYL ACETATE [] ROSMARINUS OFFICINALIS (ROSEMARY) EXTRACT [] GLYCINE SOJA (SOYBEAN) OIL [] PHAEODACTYLUM TRICORNOTUM EXTRACT [] SANTALUM ALBUM SEED EXTRACT [] PORIA COCOS SCLEROTIUM EXTRACT [] SODIUM RNA [] TOURMALINE [] DIMETHICONE SILYLATE [] DIMETHICONE [] CALCIUM CARBONATE [] MALACHITE [] PHYTOSPHINGOSINE [] CAPRYLIC/CAPRIC TRIGLYCERIDE [] ALLYL METHACRYLATES CROSSPOLYMER [] BISABOLOL [] PENTAERYTHRITYL TETRA-DI-T-BUTYL HYDROXYHYDROCINNAMATE [] ISOPROPYL TITANIUM TRIISOSTEARATE [] HYDROGENATED COTTONSEED OIL [] TIN OXIDE [] ALUMINA [] SILICA [] [+/- MICA [] TITANIUM DIOXIDE (CI 77891) [] IRON OXIDES (CI 77491, CI 77492, CI 77499)]

WARNINGS

WARNING: KEEP OUT OF EYES. STOP USE IF IRRITATION OCCURS. KEEP OUT OF REACH OF CHILDREN.

PACKAGE LABEL

PRINCIPAL DISPLAY PANEL

skin color de la mer

LA MER

THE RADIANT CONCEALER SPF 25

NT WT. 0.11 OZ/3.5 g

MAX HUBER RESEARCH LABS INC DISTR

NEW YORK, NY 10022